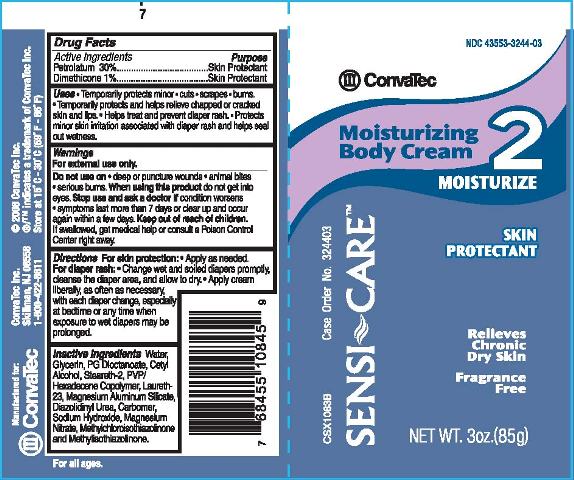 DRUG LABEL: SENSI CARE MOISTURIZING BODY
NDC: 43553-3244 | Form: CREAM
Manufacturer: ConvaTec, Inc.
Category: otc | Type: HUMAN OTC DRUG LABEL
Date: 20110414

ACTIVE INGREDIENTS: PETROLATUM 300 mg/1 g; DIMETHICONE 10 mg/1 g
INACTIVE INGREDIENTS: WATER; GLYCERIN; PROPYLENE GLYCOL DIETHYLHEXANOATE; CETYL ALCOHOL; STEARETH-2; LAURETH-23; MAGNESIUM ALUMINUM SILICATE; DIAZOLIDINYL UREA; CARBOMER 934; SODIUM HYDROXIDE; MAGNESIUM NITRATE; METHYLCHLOROISOTHIAZOLINONE; METHYLISOTHIAZOLINONE

Drug Facts

Active Ingredients

Petrolatum 30%

Dimethicone 1%

Purpose

Skin Protectant

Skin Protectant

Uses

- Temporarily protects minor
- cuts
- scrapes
- burns.

- Temporarily protects and helps relieve chapped or cracked skin and lips.
- Helps treat and prevent diaper rash.
- Protects minor skin irritation associated with diaper rash and helps seal out wetness.

Warnings

For external use only.

Do not use on

- deep or puncture wounds
- animal bites
- serious burns.

When using this product

do not get into eyes.

Stop use and ask a doctor if

- condition worsens
- symptoms last more than 7 days or clear up and occur again within a few days.

Keep out of reach of children.

If swallowed, get medical help or consult a Poison Control Center right away.

Directions

For skin protection:

- Apply as needed

For diaper rash:

- Change wet and soiled diapers promptly, cleanse the diaper area, and allow to dry.
- Apply cream liberally, as often as necessary, with each diaper change, especially at bedtime or any time when exposure to wet diapers may be prolonged.

Other Information

Store at 15oC - 30oC (59oF - 86oF).

Inactive Ingredients

Water, Glycerin, PG Dioctanoate, Cetyl Alcohol, Steareth-2, PVP/Hexadecene Copolymer, Laureth-23, Magnesium Aluminum Silicate, Diazolidinyl Urea, Carbomer, Sodium Hydroxide, Magnesium Nitrate, Methylchloroisothiazolinone and Methylisothiazolinone.

PRINCIPAL DISPLAY PANEL

NDC 43553-3244-3

ConvaTec

SENSI~CARETM

Moisturizing Body Cream 2

MOISTURIZE

SKIN PROTECTANT

Relieves Chronic Dry Skin

Fragrance Free

NET WT. 3oz.(85g)

CSX1083B Case Order No. 324403